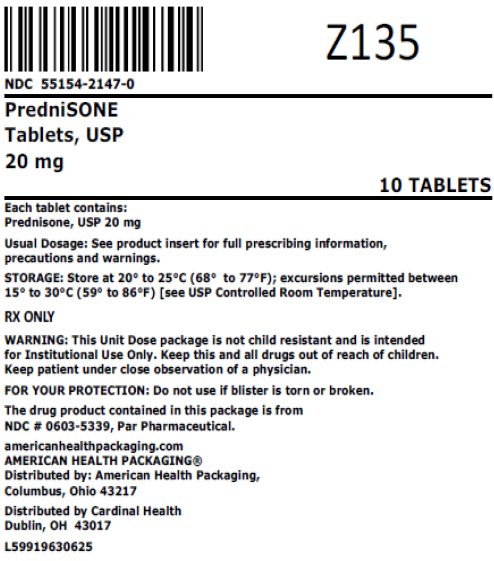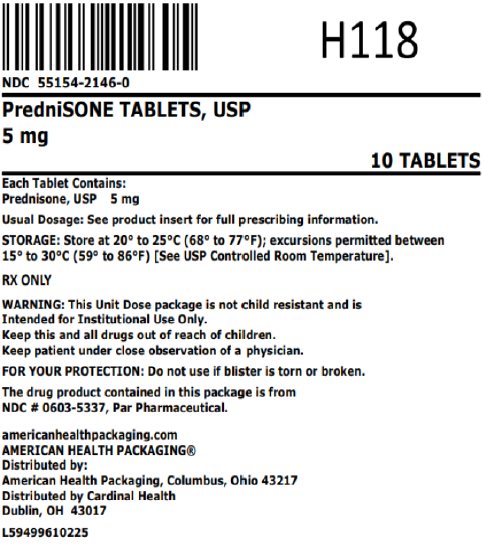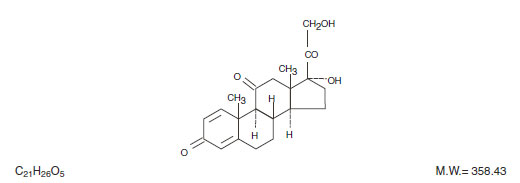 DRUG LABEL: Prednisone
NDC: 55154-2146 | Form: TABLET
Manufacturer: Cardinal Health 107, LLC
Category: prescription | Type: HUMAN PRESCRIPTION DRUG LABEL
Date: 20260127

ACTIVE INGREDIENTS: PREDNISONE 5 mg/1 1
INACTIVE INGREDIENTS: SILICON DIOXIDE; LACTOSE MONOHYDRATE; MAGNESIUM STEARATE; STARCH, CORN; SODIUM STARCH GLYCOLATE TYPE A POTATO

PredniSONE Tablets, USP

8416621/0623

Rx only

DESCRIPTION

PredniSONE Tablets contain prednisone which is a glucocorticoid. Glucocorticoids are adrenocortical steroids, both naturally occurring and synthetic, which are readily absorbed from the gastrointestinal tract. Prednisone is a white to practically white, odorless, crystalline powder. It is very slightly soluble in water; slightly soluble in alcohol, chloroform, dioxane, and methanol.

The chemical name for prednisone is pregna-1,4-diene-3,11,20-trione monohydrate, 17,21-dihydroxy-. The structural formula is represented below:

PredniSONE Tablets are available in 5 strengths: 1 mg, 2.5 mg, 5 mg, 10 mg and 20 mg.

Inactive ingredients: 1 mg — colloidal silicon dioxide, lactose monohydrate, magnesium stearate, pregelatinized starch, sodium starch glycolate; 2.5 mg — colloidal silicon dioxide, lactose monohydrate, magnesium stearate, pregelatinized starch, sodium starch glycolate; 5 mg — colloidal silicon dioxide, lactose monohydrate, magnesium stearate, pregelatinized starch, sodium starch glycolate; 10 mg — colloidal silicon dioxide, lactose monohydrate, magnesium stearate, pregelatinized starch, sodium starch glycolate; 20 mg — FD&C Yellow #6 Lake, lactose monohydrate, magnesium stearate, microcrystalline cellulose, sodium starch glycolate.

CLINICAL PHARMACOLOGY

Naturally occurring glucocorticoids (hydrocortisone and cortisone), which also have salt-retaining properties, are used as replacement therapy in adrenocortical deficiency states. Their synthetic analogs are primarily used for their potent anti-inflammatory effects in disorders of many organ systems.

Glucocorticoids cause profound and varied metabolic effects. In addition, they modify the body's immune responses to diverse stimuli.

INDICATIONS AND USAGE

PredniSONE Tablets are indicated in the following conditions:

1. Endocrine Disorders
  Primary or secondary adrenocortical insufficiency (hydrocortisone or cortisone is the first choice; synthetic analogs may be used in conjunction with mineralocorticoids where
  applicable; in infancy mineralocorticoid supplementation is of particular importance)
  Congenital adrenal hyperplasia
  Nonsuppurative thyroiditis
  Hypercalcemia associated with cancer
2. Rheumatic Disorders
  As adjunctive therapy for short-term administration (to tide the patient over an acute episode
  or exacerbation) in:
  Psoriatic arthritis
  Rheumatoid arthritis, including juvenile rheumatoid arthritis (selected cases may require low-dose maintenance therapy)
  Ankylosing spondylitis
  Acute and subacute bursitis
  Acute nonspecific tenosynovitis
  Acute gouty arthritis
  Post-traumatic osteoarthritis
  Synovitis of osteoarthritis
  Epicondylitis
3. Collagen Diseases
  During an exacerbation or as maintenance therapy in selected cases of:
  Systemic lupus erythematosus
  Systemic dermatomyositis (polymyositis)
  Acute rheumatic carditis
4. Dermatologic Diseases
  Pemphigus
  Bullous dermatitis herpetiformis
  Severe erythema multiforme (Stevens-Johnson syndrome)
  Exfoliative dermatitis
  Mycosis fungoides
  Severe psoriasis
  Severe seborrheic dermatitis
5. Allergic States
  Control of severe or incapacitating allergic conditions intractable to adequate trials of conventional treatment:
  Seasonal or perennial allergic rhinitis
  Bronchial asthma
  Contact dermatitis
  Atopic dermatitis
  Serum sickness
  Drug hypersensitivity reactions
6. Ophthalmic Diseases
  Severe acute and chronic allergic and inflammatory processes involving the eye and its adnexa such as:
  Allergic corneal marginal ulcers
  Herpes zoster ophthalmicus
  Anterior segment inflammation
  Diffuse posterior uveitis and choroiditis
  Sympathetic ophthalmia
  Allergic conjunctivitis
  Keratitis
  Chorioretinitis
  Optic neuritis
  Iritis and iridocyclitis
7. Respiratory Diseases
  Symptomatic sarcoidosis
  Loeffler's syndrome not manageable by other means
  Berylliosis
  Aspiration pneumonitis
  Fulminating or disseminated pulmonary tuberculosis when used concurrently with appropriate antituberculous chemotherapy
8. Hematologic Disorders
  Idiopathic thrombocytopenic purpura in adults
  Secondary thrombocytopenia in adults
  Acquired (autoimmune) hemolytic anemia
  Erythroblastopenia (RBC anemia)
  Congenital (erythroid) hypoplastic anemia
9. Neoplastic Diseases
  For palliative management of:
  Leukemias and lymphomas in adults
  Acute leukemia of childhood
10. Edematous States
  To induce a diuresis or remission of proteinuria in the nephrotic syndrome, without uremia, of
  the idiopathic type or that due to lupus erythematosus
11. Gastrointestinal Diseases
  To tide the patient over a critical period of the disease in:
  Ulcerative colitis
  Regional enteritis
12. Miscellaneous
  Tuberculous meningitis with subarachnoid block or impending block when used concurrently
  with appropriate antituberculous chemotherapy
  Trichinosis with neurologic or myocardial involvement

CONTRAINDICATIONS

Prednisone tablets are contraindicated in systemic fungal infections and known hypersensitivity to components.

WARNINGS

General

Rare instances of anaphylactoid reactions have occurred in patients receiving corticosteroid therapy (see ADVERSE REACTIONS: Allergic Reactions).

Increased dosage of rapidly acting corticosteroids is indicated in patients on corticosteroid therapy subjected to any unusual stress before, during and after the stressful situation.

Cardio-Renal

Average and large doses of hydrocortisone or cortisone can cause elevation of blood pressure, salt and water retention, and increased excretion of potassium. These effects are less likely to occur with the synthetic derivatives except when used in large doses. Dietary salt restriction and potassium supplementation may be necessary. All corticosteroids increase calcium excretion.

Literature reports suggest an apparent association between use of corticosteroids and left ventricular free wall rupture after a recent myocardial infarction; therefore, therapy with corticosteroids should be used with great caution in these patients.

Endocrine

Corticosteroids can produce reversible hypothalamic-pituitary adrenal (HPA) axis suppression with the potential for corticosteroid insufficiency after withdrawal of treatment. Adrenocortical insufficiency may result from too rapid withdrawal of corticosteroids and may be minimized by gradual reduction of dosage. This type of relative insufficiency may persist for up to 12 months after discontinuation of therapy; therefore, in any situation of stress occurring during that period, hormone therapy should be reinstituted. If the patient is receiving steroids already, dosage may have to be increased.

Metabolic clearance of corticosteroids is decreased in hypothyroid patients and increased in hyperthyroid patients. Changes in thyroid status of the patient may necessitate adjustment in dosage.

Infection

General

Patients who are on corticosteroids are more susceptible to infections than are healthy individuals. There may be decreased resistance and inability to localize infection when corticosteroids are used. Infection with any pathogen (viral, bacterial, fungal, protozoan or helminthic) in any location of the body may be associated with the use of corticosteroids alone or in combination with other immunosuppressive agents that affect cellular immunity, humoral immunity, or neutrophil function. ^1These infections may be mild, but may be severe and at times fatal. With increasing doses of corticosteroids, the rate of occurrence of infectious complications increases. ^2Corticosteroids may also mask some signs of current infection.

Fungal Infections

Corticosteroids may exacerbate systemic fungal infections and therefore should not be used in the presence of such infections unless they are needed to control life-threatening drug reactions. There have been cases reported in which concomitant use of amphotericin B and hydrocortisone was followed by cardiac enlargement and congestive heart failure (see PRECAUTIONS: Drug Interactions: Amphotericin B Injection and Potassium-Depleting Agents).

Special Pathogens

Latent disease may be activated or there may be an exacerbation of intercurrent infections due to pathogens, including those caused by Amoeba, Candida, Cryptococcus, Mycobacterium, Nocardia, Pneumocystis, Toxoplasma.

It is recommended that latent amebiasis or active amebiasis be ruled out before initiating corticosteroid therapy in any patient who has spent time in the tropics or any patient with unexplained diarrhea.

Similarly, corticosteroids should be used with great care in patients with known or suspected Strongyloides (threadworm) infestation. In such patients, corticosteroid-induced immunosuppression may lead to Strongyloides hyperinfection and dissemination with widespread larval migration, often accompanied by severe enterocolitis and potentially fatal gram-negative septicemia.

Corticosteroids should not be used in cerebral malaria.

Tuberculosis

The use of prednisone in active tuberculosis should be restricted to those cases of fulminating or disseminated tuberculosis in which the corticosteroid is used for management of the disease in conjunction with an appropriate antituberculous regimen.

If corticosteroids are indicated in patients with latent tuberculosis or tuberculin reactivity, close observation is necessary as reactivation of the disease may occur. During prolonged corticosteroid therapy, these patients should receive chemoprophylaxis.

Vaccination

Administration of live or live, attenuated vaccines is contraindicated in patients receiving immunosuppressive doses of corticosteroids. Killed or inactivated vaccines may be administered. However, the response to such vaccines may be diminished and cannot be predicted. Indicated immunization procedures may be undertaken in patients receiving nonimmunosuppressive doses of corticosteroids as replacement therapy (e.g., for Addison’s disease).

Viral Infections

Chickenpox and measles can have a more serious or even fatal course in pediatric and adult patients on corticosteroids. In pediatric and adult patients who have not had these diseases, particular care should be taken to avoid exposure. How the dose, route and duration of corticosteroid administration affect the risk of developing a disseminated infection is not known. The contribution of the underlying disease and/or prior corticosteroid treatment to the risk is also not known. If exposed to chickenpox, prophylaxis with varicella zoster immune globulin (VZIG) may be indicated. If exposed to measles, prophylaxis with pooled intramuscular immunoglobulin (IG) may be indicated. (See the respective package inserts for complete VZIG and IG prescribing information.) If chickenpox develops, treatment with antiviral agents may be considered.

Ophthalmic

Use of corticosteroids may produce posterior subcapsular cataracts, glaucoma with possible damage to the optic nerves, and may enhance the establishment of secondary ocular infections due to bacteria, fungi or viruses. The use of oral corticosteroids is not recommended in the treatment of optic neuritis and may lead to an increase in the risk of new episodes. Corticosteroids should not be used in active ocular herpes simplex because of possible corneal perforation.

PRECAUTIONS

General Precautions

The lowest possible dose of corticosteroids should be used to control the condition under treatment. When reduction in dosage is possible, the reduction should be gradual.

Since complications of treatment with glucocorticoids are dependent on the size of the dose and the duration of treatment, a risk/benefit decision must be made in each individual case as to dose and duration of treatment and as to whether daily or intermittent therapy should be used.

Kaposi’s sarcoma has been reported to occur in patients receiving corticosteroid therapy, most often for chronic conditions. Discontinuation of corticosteroids may result in clinical improvement.

Cardio-Renal

As sodium retention with resultant edema and potassium loss may occur in patients receiving corticosteroids, these agents should be used with caution in patients with congestive heart failure, hypertension, or renal insufficiency.

Endocrine

Drug-induced secondary adrenocortical insufficiency may be minimized by gradual reduction of dosage. This type of relative insufficiency may persist for up to 12 months after discontinuation of therapy following large doses for prolonged periods; therefore, in any situation of stress occurring during that period, hormone therapy should be reinstituted. Since mineralocorticoid secretion may be impaired, salt and/or a mineralocorticoid should be administered concurrently.

There is an enhanced effect of corticosteroids on patients with hypothyroidism.

Gastrointestinal

Steroids should be used with caution in active or latent peptic ulcers, diverticulitis, fresh intestinal anastomoses, and nonspecific ulcerative colitis, since they may increase the risk of a perforation.

Signs of peritoneal irritation following gastrointestinal perforation in patients receiving corticosteroids may be minimal or absent.

There is an enhanced effect due to decreased metabolism of corticosteroids in patients with cirrhosis.

Musculoskeletal

Corticosteroids decrease bone formation and increase bone resorption both through their effect on calcium regulation (i.e., decreasing absorption and increasing excretion) and inhibition of osteoblast function. This, together with a decrease in the protein matrix of the bone secondary to an increase in protein catabolism, and reduced sex hormone production, may lead to inhibition of bone growth in pediatric patients and the development of osteoporosis at any age. Growth and development of infants and children on prolonged corticosteroid therapy should be carefully observed. Special consideration should be given to patients at increased risk of osteoporosis (e.g., postmenopausal women) before initiating corticosteroid therapy.

Inclusion of therapy for osteoporosis prevention or treatment should be considered. To minimize the risk of glucocortoicoid-induced bone loss, the smallest possible effective dosage and duration should be used. Lifestyle modification to reduce the risk of osteoporosis (e.g., cigarette smoking cessation, limitation of alcohol consumption, participation in weight-bearing exercise for 30-60 minutes daily) should be encouraged. Calcium and vitamin D supplementation, bisphosphonate (e.g., alendronate, risedronate), and a weight-bearing exercise program that maintains muscle mass are suitable first-line therapies aimed at reducing the risk of adverse bone effects. Current recommendations suggest that all interventions be initiated in any patient in whom glucocorticoid therapy with at least the equivalent of 5 mg of prednisone for at least 3 months is anticipated; in addition, sex hormone replacement therapy (combined estrogen and progestin in women; testosterone in men) should be offered to such patients who are hypogonadal or in whom replacement is otherwise clinically indicated and biphosphonate therapy should be initiated (if not already) if bone mineral density (BMD) of the lumbar spine and/or hip is below normal.

Neuro-Psychiatric

Although controlled clinical trials have shown corticosteroids to be effective in speeding the resolution of acute exacerbations of multiple sclerosis, they do not show that they affect the ultimate outcome or natural history of the disease. The studies do show that relatively high doses of corticosteroids are necessary to demonstrate a significant effect. (See DOSAGE AND ADMINISTRATION: Multiple Sclerosis.)

An acute myopathy has been observed with the use of high doses of corticosteroids, most often occurring in patients with disorders of neuromuscular transmission (e.g., myasthenia gravis), or in patients receiving concomitant therapy with neuromuscular blocking drugs (e.g., pancuronium). This acute myopathy is generalized, may involve ocular and respiratory muscles, and may result in quadriparesis. Elevation of creatinine kinase may occur. Clinical improvement or recovery after stopping corticosteroids may require weeks to years.

Psychiatric derangements may appear when corticosteroids are used, ranging from euphoria, insomnia, mood swings, personality changes, and severe depression, to frank psychotic manifestations. Also, existing emotional instability or psychotic tendencies may be aggravated by corticosteroids.

Ophthalmic

Intraocular pressure may become elevated in some individuals. If steroid therapy is continued for more than 6 weeks, intraocular pressure should be monitored.

Information for Patients

Patients should be warned not to discontinue the use of corticosteroids abruptly or without medical supervision. As prolonged use may cause adrenal insufficiency and make patients dependent on corticosteroids, they should advise any medical attendants that they are taking corticosteroids and they should seek medical advice at once should they develop an acute illness including fever or other signs of infection. Following prolonged therapy, withdrawal of corticosteroids may result in symptoms of the corticosteroid withdrawal syndrome including, myalgia, arthralgia, and malaise.

Persons who are on corticosteroids should be warned to avoid exposure to chickenpox or measles. Patients should also be advised that if they are exposed, medical advice should be sought without delay.

Drug Interactions

Amphotericin B Injection and Potassium-Depleting Agents

When corticosteroids are administered concomitantly with potassium-depleting agents (e.g., amphotericin B, diuretics), patients should be observed closely for development of hypokalemia. In addition, there have been cases reported in which concomitant use of amphotericin B and hydrocortisone was followed by cardiac enlargement and congestive heart failure.

Antibiotics

Macrolide antibiotics have been reported to cause a significant decrease in corticosteroid clearance (see PRECAUTIONS: Drug Interactions: Hepatic Enzyme Inducers, Inhibitors and Substrates).

Anticholinesterases

Concomitant use of anticholinesterase agents (e.g., neostigmine, pyridostigmine) and corticosteroids may produce severe weakness in patients with myasthenia gravis. If possible, anticholinesterase agents should be withdrawn at least 24 hours before initiating corticosteroid therapy. If concomitant therapy must occur, it should take place under close supervision and the need for respiratory support should be anticipated.

Anticoagulants, Oral

Co-administration of corticosteroids and warfarin usually results in inhibition of response to warfarin, although there have been some conflicting reports. Therefore, coagulation indices should be monitored frequently to maintain the desired anticoagulant effect.

Antidiabetics

Because corticosteroids may increase blood glucose concentrations, dosage adjustments of antidiabetic agents may be required.

Antitubercular drugs

Serum concentrations of isoniazid may be decreased.

Bupropion

Since systemic steroids, as well as bupropion, can lower the seizure threshold, concurrent administration should be undertaken only with extreme caution; low initial dosing and small gradual increases should be employed.

Cholestyramine

Cholestyramine may increase the clearance of corticosteroids.

Cyclosporine

Increased activity of both cyclosporine and corticosteroids may occur when the two are used concurrently. Convulsions have been reported with this concurrent use.

Digitalis Glycosides

Patients on digitalis glycosides may be at increased risk of arrhythmias due to hypokalemia.

Estrogens, Including Oral Contraceptives

Estrogens may decrease the hepatic metabolism of certain corticosteroids, thereby increasing their effect.

Fluoroquinolones

Post-marketing surveillance reports indicate that the risk of tendon rupture may be increased in patients receiving concomitant fluoroquinolones (e.g., ciprofloxacin, levofloxacin) and corticosteroids, especially in the elderly. Tendon rupture can occur during or after treatment with quinolones.

Hepatic Enzyme Inducers, Inhibitors and Substrates

Drugs which induce cytochrome P450 3A4 (CYP 3A4) enzyme activity (e.g., barbiturates, phenytoin, carbamazepine, rifampin) may enhance the metabolism of corticosteroids and require that the dosage of the corticosteroid be increased. Drugs which inhibit CYP 3A4 (e.g., ketoconazole, itraconazole, ritonavir, indinavir, macrolide antibiotics such as erythromycin) have the potential to result in increased plasma concentrations of corticosteroids. Glucocorticoids are moderate inducers of CYP 3A4. Co-administration with other drugs that are metabolized by CYP 3A4 (e.g., indinavir, erythromycin) may increase their clearance, resulting in decreased plasma concentration.

Ketoconazole

Ketoconazole has been reported to decrease the metabolism of certain corticosteroids by up to 60%, leading to increased risk of corticosteroid side effects. In addition, ketoconazole alone can inhibit adrenal corticosteroid synthesis and may cause adrenal insufficiency during corticosteroid withdrawal.

Nonsteroidal Anti-Inflammatory Agents (NSAIDS)

Concomitant use of aspirin (or other nonsteroidal anti-inflammatory agents) and corticosteroids increases the risk of gastrointestinal side effects. Aspirin should be used cautiously in conjunction with corticosteroids in hypoprothrombinemia. The clearance of salicylates may be increased with concurrent use of corticosteroids; this could lead to decreased salicylate serum levels or increase the risk of salicylate toxicity when corticosteroid is withdrawn.

Phenytoin

In post-marketing experience, there have been reports of both increases and decreases in phenytoin levels with dexamethasone co-administration, leading to alterations in seizure control. Phenytoin has been demonstrated to increase the hepatic metabolism of corticosteroids, resulting in a decreased therapeutic effect of the corticosteroid.

Quetiapine

Increased doses of quetiapine may be required to maintain control of symptoms of schizophrenia in patients receiving a glucocorticoid, a hepatic enzyme inducer.

Skin Tests

Corticosteroids may suppress reactions to skin tests.

Thalidomide

Co-administration with thalidomide should be employed cautiously, as toxic epidermal necrolysis has been reported with concomitant use.

Vaccines

Patients on corticosteroid therapy may exhibit a diminished response to toxoids and live or inactivated vaccines due to inhibition of antibody response. Corticosteroids may also potentiate the replication of some organisms contained in live attenuated vaccines. Routine administration of vaccines or toxoids should be deferred until corticosteroid therapy is discontinued if possible (see WARNINGS: Infection: Vaccination).

Carcinogenesis, Mutagenesis, Impairment of Fertility

No adequate studies have been conducted in animals to determine whether corticosteroids have a potential for carcinogenesis or mutagenesis. Steroids may increase or decrease motility and number of spermatozoa in some patients.

Pregnancy

Teratogenic Effects

Pregnancy Category C

Corticosteroids have been shown to be teratogenic in many species when given in doses equivalent to the human dose. Animal studies in which corticosteroids have been given to pregnant mice, rats, and rabbits have yielded an increased incidence of cleft palate in the offspring. There are no adequate and well-controlled studies in pregnant women. Corticosteroids should be used during pregnancy only if the potential benefit justifies the potential risk to the fetus. Infants born to mothers who have received substantial doses of corticosteroids during pregnancy should be carefully observed for signs of hypoadrenalism.

Nursing Mothers

Systemically administered corticosteroids appear in human milk and could suppress growth, interfere with endogenous corticosteroid production, or cause other untoward effects. Because of the potential for serious adverse reactions in nursing infants from corticosteroids, a decision should be made whether to discontinue nursing or to discontinue the drug, taking into account the importance of the drug to the mother.

Pediatric Use

The efficacy and safety of corticosteroids in the pediatric population are based on the well-established course of effect of corticosteroids, which is similar in pediatric and adult populations. Published studies provide evidence of efficacy and safety in pediatric patients for the treatment of nephrotic syndrome (patients >2 years of age), and aggressive lymphomas and leukemias (patients >1 month of age). Other indications for pediatric use of corticosteroids, e.g., severe asthma and wheezing, are based on adequate and well-controlled trials conducted in adults, on the premises that the course of the diseases and their pathophysiology are considered to be substantially similar in both populations.

The adverse effects of corticosteroids in pediatric patients are similar to those in adults (see ADVERSE REACTIONS). Like adults, pediatric patients should be carefully observed with frequent measurements of blood pressure, weight, height, intraocular pressure, and clinical evaluation for the presence of infection, psychosocial disturbances, thromboembolism, peptic ulcers, cataracts, and osteoporosis. Pediatric patients who are treated with corticosteroids by any route, including systemically administered corticosteroids, may experience a decrease in their growth velocity. This negative impact of corticosteroids on growth has been observed at low systemic doses and in the absence of laboratory evidence of hypothalamic-pituitary-adrenal (HPA) axis suppression (i.e., cosyntropin stimulation and basal cortisol plasma levels). Growth velocity may therefore be a more sensitive indicator of systemic corticosteroid exposure in pediatric patients than some commonly used tests of HPA axis function. The linear growth of pediatric patients treated with corticosteroids should be monitored, and the potential growth effects of prolonged treatment should be weighed against clinical benefits obtained and the availability of treatment alternatives. In order to minimize the potential growth effects of corticosteroids, pediatric patients should be titrated to the lowest effective dose.

Geriatric Use

Clinical studies did not include sufficient numbers of subjects aged 65 and over to determine whether they respond differently from younger subjects. Other reported clinical experience has not identified differences in responses between the elderly and younger patients. In general, dose selection for an elderly patient should be cautious, usually starting at the low end of the dosing range, reflecting the greater frequency of decreased hepatic, renal, or cardiac function, and of concomitant disease or other drug therapy. In particular, the increased risk of diabetes mellitus, fluid retention and hypertension in elderly patients treated with corticosteroids should be considered.

ADVERSE REACTIONS

(listed alphabetically, under each subsection)
The following adverse reactions have been reported with prednisone or other corticosteroids:

Allergic Reactions
anaphylactoid or hypersensitivity reactions, anaphylaxis, angioedema.

Cardiovascular System
bradycardia, cardiac arrest, cardiac arrhythmias, cardiac enlargement, circulatory collapse, congestive heart failure, ECG changes caused by potassium deficiency, edema, fat embolism, hypertension or aggravation of hypertension, hypertrophic cardiomyopathy in premature infants, myocardial rupture following recent myocardial infarction (see WARNINGS: Cardio-Renal), necrotizing angiitis, pulmonary edema, syncope, tachycardia, thromboembolism, thrombophlebitis, vasculitis.

Dermatologic
acne, acneiform eruptions, allergic dermatitis, alopecia, angioedema, angioneurotic edema, atrophy and thinning of skin, dry scaly skin, ecchymoses and petechiae (bruising), erythema, facial edema, hirsutism, impaired wound healing, increased sweating, Karposi’s sarcoma (see PRECAUTIONS: General Precautions), lupus erythematosus-like lesions, perineal irritation, purpura, rash, striae, subcutaneous fat atrophy, suppression of reactions to skin tests, striae, telangiectasis, thin fragile skin, thinning scalp hair, urticaria.

Endocrine
Adrenal insufficiency-greatest potential caused by high potency glucocorticoids with long duration of action (associated symptoms include; arthralgias, buffalo hump, dizziness, life-threatening hypotension, nausea, severe tiredness or weakness), amenorrhea, postmenopausal bleeding or other menstrual irregularities, decreased carbohydrate and glucose tolerance, development of cushingoid state, diabetes mellitus (new onset or manifestations of latent), glycosuria, hyperglycemia, hypertrichosis, hyperthyroidism (see WARNINGS: Endocrine), hypothyroidism, increased requirements for insulin or oral hypoglycemic agents in diabetics, lipids abnormal, moon face, negative nitrogen balance caused by protein catabolism, secondary adrenocortical and pituitary unresponsiveness (particularly in times of stress, as in trauma, surgery or illness) (see WARNINGS: Endocrine), suppression of growth in pediatric patients.

Fluid and Electrolyte Disturbances
congestive heart failure in susceptible patients, fluid retention, hypokalemia, hypokalemic alkalosis, metabolic alkalosis, hypotension or shock-like reaction, potassium loss, sodium retention with resulting edema.

Gastrointestinal
abdominal distention, abdominal pain, anorexia which may result in weight loss, constipation, diarrhea, elevation in serum liver enzyme levels (usually reversible upon discontinuation), gastric irritation, hepatomegaly, increased appetite and weight gain, nausea, oropharyngeal candidiasis, pancreatitis, peptic ulcer with possible perforation and hemorrhage, perforation of the small and large intestine (particularly in patients with inflammatory bowel disease), ulcerative esophagitis, vomiting.

Hematologic
anemia, neutropenia (including febrile neutropenia).

Metabolic
negative nitrogen balance due to protein catabolism.

Musculoskeletal
arthralgias, aseptic necrosis of femoral and humeral heads, increase risk of fracture, loss of muscle mass, muscle weakness, myalgias, osteopenia, osteoporosis (see PRECAUTIONS: Musculoskeletal), pathologic fracture of long bones, steroid myopathy, tendon rupture (particularly of the Achilles tendon), vertebral compression fractures.

Neurological/Psychiatric
amnesia, anxiety, benign intracranial hypertension, convulsions, delirium, dementia (characterized by deficits in memory retention, attention, concentration, mental speed and efficiency, and occupational performance), depression, dizziness, EEG abnormalities, emotional instability and irritability, euphoria, hallucinations, headache, impaired cognition, incidence of severe psychiatric symptoms, increased intracranial pressure with papilledema (pseudotumor cerebri) usually following discontinuation of treatment, increased motor activity, insomnia, ischemic neuropathy, long-term memory loss, mania, mood swings, neuritis, neuropathy, paresthesia, personality changes, psychiatric disorders including steroid psychoses or aggravation of pre-existing psychiatric conditions, restlessness, schizophrenia, verbal memory loss, vertigo, withdrawn behavior.

Ophthalmic
blurred vision, cataracts (including posterior subcapsular cataracts), central serous chorioretinopathy, establishment of secondary bacterial, fungal and viral infections, exophthalmos, glaucoma, increased intraocular pressure (see PRECAUTIONS: Ophthalmic), optic nerve damage, papilledema.

Other
abnormal fat deposits, aggravation/masking of infections, decreased resistance to infection (see WARNINGS: Infection), hiccups, immunosuppression, increased or decreased motility and number of spermatozoa, malaise, insomnia, moon face, pyrexia.

DOSAGE AND ADMINISTRATION

Gastric irritation may be reduced if taken before, during, or immediately after meals or with food or milk.

The maximal activity of the adrenal cortex is between 2 am and 8 am, and it is minimal between 4 pm and midnight. Exogenous corticosteroids suppress adrenocorticoid activity the least when given at the time of maximal activity (am) for single dose administration. Therefore, it is recommended that prednisone be administered in the morning prior to 9 am and when large doses are given, administration of antacids between meals to help prevent peptic ulcers. Multiple dose therapy should be evenly distributed in evenly spaced intervals throughout the day.

Dietary salt restriction may be advisable in patients.

Do not stop taking this medicine without first talking to your doctor. Avoid abrupt withdraw of therapy.

The initial dosage of PredniSONE Tablets may vary from 5 mg to 60 mg per day, depending on the specific disease entity being treated. In situations of less severity lower doses will generally suffice, while in selected patients higher initial doses may be required. The initial dosage should be maintained or adjusted until a satisfactory response is noted. If after a reasonable period of time there is a lack of satisfactory clinical response, PredniSONE should be discontinued and the patient transferred to other appropriate therapy. IT SHOULD BE EMPHASIZED THAT DOSAGE REQUIREMENTS ARE VARIABLE AND MUST BE INDIVIDUALIZED ON THE BASIS OF THE DISEASE UNDER TREATMENT AND THE RESPONSE OF THE PATIENT. After a favorable response is noted, the proper maintenance dosage should be determined by decreasing the initial drug dosage in small increments at appropriate time intervals until the lowest dosage which will maintain an adequate clinical response is reached. It should be kept in mind that constant monitoring is needed in regard to drug dosage. Included in the situations which may make dosage adjustments necessary are changes in clinical status secondary to remissions or exacerbations in the disease process, the patient's individual drug responsiveness, and the effect of patient exposure to stressful situations not directly related to the disease entity under treatment; in this latter situation, it may be necessary to increase the dosage of PredniSONE for a period of time consistent with the patient's condition. If after long-term therapy the drug is to be stopped, it is recommended that it be withdrawn gradually rather than abruptly.

Multiple Sclerosis

In the treatment of acute exacerbations of multiple sclerosis daily doses of 200 mg of prednisolone for a week followed by 80 mg every other day for 1 month have been shown to be effective. (Dosage range is the same for prednisone and prednisolone.)

Alternate day therapy is a corticosteroid dosing regimen in which twice the usual daily dose of corticoid is administered every other morning. The purpose of this mode of therapy is to provide the patient requiring long-term pharmacologic dose treatment with the beneficial effects of corticoids while minimizing certain undesirable effects, including pituitary-adrenal suppression, the Cushingoid state, corticoid withdrawal symptoms, and growth suppression in children.

The rationale for this treatment schedule is based on two major premises: (a) the anti-inflammatory or therapeutic effect of corticoids persists longer than their physical presence and metabolic effects and (b) administration of the corticosteroid every other morning allows for re-establishment of more nearly normal hypothalamic-pituitary-adrenal (HPA) activity on the off-steroid day.

A brief review of the HPA physiology may be helpful in understanding this rationale. Acting primarily through the hypothalamus a fall in free cortisol stimulates the pituitary gland to produce increasing amounts of corticotropin (ACTH) while a rise in free cortisol inhibits ACTH secretion. Normally the HPA system is characterized by diurnal (circadian) rhythm. Serum levels of ACTH rise from a low point about 10 pm to a peak level about 6 am. Increasing levels of ACTH stimulate adrenocortical activity resulting in a rise in plasma cortisol with maximal levels occurring between 2 am and 8 am. This rise in cortisol dampens ACTH production and in turn adrenocortical activity. There is a gradual fall in plasma corticoids during the day with lowest levels occurring about midnight.

The diurnal rhythm of the HPA axis is lost in Cushing's disease, a syndrome of adrenocortical hyperfunction characterized by obesity with centripetal fat distribution, thinning of the skin with easy bruisability, muscle wasting with weakness, hypertension, latent diabetes, osteoporosis, electrolyte imbalance, etc. The same clinical findings of hyperadrenocorticism may be noted during long-term pharmacologic dose corticoid therapy administered in conventional daily divided doses. It would appear, then, that a disturbance in the diurnal cycle with maintenance of elevated corticoid values during the night may play a significant role in the development of undesirable corticoid effects. Escape from these constantly elevated plasma levels for even short periods of time may be instrumental in protecting against undesirable pharmacologic effects.

During conventional pharmacologic dose corticosteroid therapy, ACTH production is inhibited with subsequent suppression of cortisol production by the adrenal cortex. Recovery time for normal HPA activity is variable depending upon the dose and duration of treatment. During this time the patient is vulnerable to any stressful situation. Although it has been shown that there is considerably less adrenal suppression following a single morning dose of prednisolone (10 mg) as opposed to a quarter of that dose administered every 6 hours, there is evidence that some suppressive effect on adrenal activity may be carried over into the following day when pharmacologic doses are used. Further, it has been shown that a single dose of certain corticosteroids will produce adrenocortical suppression for two or more days. Other corticoids, including methylprednisolone, hydrocortisone, prednisone, and prednisolone, are considered to be short acting (producing adrenocortical suppression for 1¼ to 1½ days following a single dose) and thus are recommended for alternate day therapy.

The following should be kept in mind when considering alternate day therapy:

1. Basic principles and indications for corticosteroid therapy should apply. The benefits of alternate day therapy should not encourage the indiscriminate use of steroids.
2. Alternate day therapy is a therapeutic technique primarily designed for patients in whom long-term pharmacologic corticoid therapy is anticipated.
3. In less severe disease processes in which corticoid therapy is indicated, it may be possible to initiate treatment with alternate day therapy. More severe disease states usually will require daily divided high dose therapy for initial control of the disease process. The initial suppressive dose level should be continued until satisfactory clinical response is obtained, usually four to ten days in the case of many allergic and collagen diseases. It is important to keep the period of initial suppressive dose as brief as possible particularly when subsequent use of alternate day therapy is intended. Once control has been established, two courses are available: (a) change to alternate day therapy and then gradually reduce the amount of corticoid given every other day or (b) following control of the disease process reduce the daily dose of corticoid to the lowest effective level as rapidly as possible and then change over to an alternate day schedule. Theoretically, course (a) may be preferable.
4. Because of the advantages of alternate day therapy, it may be desirable to try patients on this form of therapy who have been on daily corticoids for long periods of time (e.g., patients with rheumatoid arthritis). Since these patients may already have a suppressed HPA axis, establishing them on alternate day therapy may be difficult and not always successful. However, it is recommended that regular attempts be made to change them over. It may be helpful to triple or even quadruple the daily maintenance dose and administer this every other day rather than just doubling the daily dose if difficulty is encountered. Once the patient is again controlled, an attempt should be made to reduce this dose to a minimum.
5. As indicated above, certain corticosteroids, because of their prolonged suppressive effect on adrenal activity, are not recommended for alternate day therapy (e.g., dexamethasone and betamethasone).
6. The maximal activity of the adrenal cortex is between 2 am and 8 am, and it is minimal between 4 pm and midnight. Exogenous corticosteroids suppress adrenocortical activity the least, when given at the time of maximal activity (am).
7. In using alternate day therapy it is important, as in all therapeutic situations to individualize and tailor the therapy to each patient. Complete control of symptoms will not be possible in all patients. An explanation of the benefits of alternate day therapy will help the patient to understand and tolerate the possible flare-up in symptoms which may occur in the latter part of the off-steroid day. Other symptomatic therapy may be added or increased at this time if needed.
8. In the event of an acute flare-up of the disease process, it may be necessary to return to a full suppressive daily divided corticoid dose for control. Once control is again established alternate day therapy may be re-instituted.
9. Although many of the undesirable features of corticosteroid therapy can be minimized by alternate day therapy, as in any therapeutic situation, the physician must carefully weigh the benefit-risk ratio for each patient in whom corticoid therapy is being considered.

HOW SUPPLIED

PredniSONE Tablets are available in the following strengths and package sizes:

5 mg (white, round, scored, debossed “5094” on one side and debossed “V” on the reverse side)

Overbagged with 10 tablets per bag, NDC 55154-2146-0

20 mg (peach, round, scored, debossed “5092” on one side and debossed “V” on the reverse side)

Overbagged with 10 tablets per bag, NDC 55154-2147-0

WARNING: These Unit Dose packages are not child resistant and are Intended for Institutional Use Only. Keep this and all drugs out of the reach of children.

STORAGE AND HANDLING

Store at 20° to 25°C (68° to 77°F) [see USP Controlled Room Temperature].

FOR YOUR PROTECTION: Do not use if blister is torn or broken.

REFERENCES

1. Fekety R. Infections associated with corticosteroids and immunosuppressive therapy. In: Gorbach SL, Bartlett JG, Blacklow NR, eds. Infectious Diseases. Philadelphia: WBSaunders Company 1992:1050-1.
2. Stuck AE, Minder CE, Frey FJ. Risk of infectious complications in patients taking glucocorticoids. Rev Infect Dis1989:11(6):954-63.

PACKAGING INFORMATION
American Health Packaging unit dose blisters contain drug product from Par Pharmaceutical

Distributed by:
American Health Packaging
Columbus, OH 43217

Distributed By:

Cardinal Health

Dublin, OH 43017

L59499610225

L59919630625

8416621/0623

Package/Label Display Panel

NDC 55154-2146-0

PredniSONE TABLETS, USP

5 mg

10 TABLETS

Package/Label Display Panel

NDC 55154-2147-0

PredniSONE

Tablets, USP

20 mg

10 TABLETS